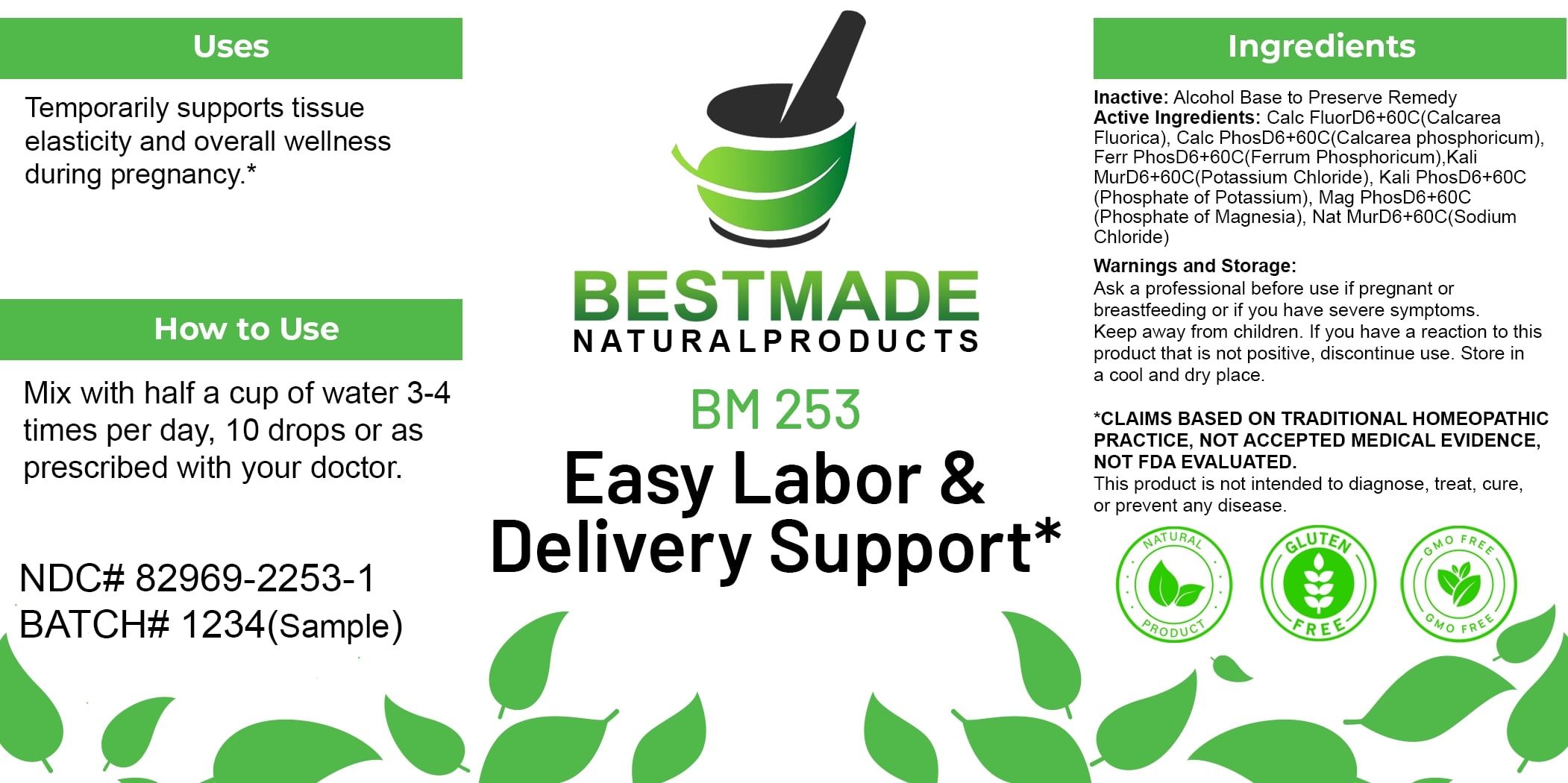 DRUG LABEL: Bestmade Natural Products BM253
NDC: 82969-2253 | Form: LIQUID
Manufacturer: Bestmade Natural Products
Category: homeopathic | Type: HUMAN OTC DRUG LABEL
Date: 20250306

ACTIVE INGREDIENTS: TRIBASIC CALCIUM PHOSPHATE 30 [hp_C]/30 [hp_C]; FERROSOFERRIC PHOSPHATE 30 [hp_C]/30 [hp_C]; POTASSIUM CHLORIDE 30 [hp_C]/30 [hp_C]; CALCIUM FLUORIDE 30 [hp_C]/30 [hp_C]; DIBASIC POTASSIUM PHOSPHATE 30 [hp_C]/30 [hp_C]; MAGNESIUM PHOSPHATE, DIBASIC TRIHYDRATE 30 [hp_C]/30 [hp_C]; SODIUM CHLORIDE 30 [hp_C]/30 [hp_C]
INACTIVE INGREDIENTS: ALCOHOL 30 [hp_C]/30 [hp_C]

BM253

DOSAGE AND ADMINISTRATION

How to Use

Mix with half a cup of water 3-4 times per day, 10 drops or as prescribed with your doctor.

INACTIVE INGREDIENT

Ingredients

Inactive: Alcohol Base to Preserve Remedy

ACTIVE INGREDIENT

Active Ingredients: Calc Fluor D6+60C (Calcarea Fluorica), Calc Phos D6+60C (Calcarea phosphoricum), Ferr Phos D6+60C (Ferrum Phosphoricum), Kali Mur D6+60C (Potassium Chloride), Kali Phos D6+60C (Phosphate of Potassium), Mag Phos D6+60C (Phosphate of Magnesia), Nat Mur D6+60C (Sodium Chloride)

Uses

Temporarily supports tissue elasticity and overall wellness during pregnancy.*

*CLAIMS BASED ON TRADITIONAL HOMEOPATHIC PRACTICE, NOT ACCEPTED MEDICAL EVIDENCE, NOT FDA EVALUATED.

This product is not intended to diagnose, treat, cure, or prevent any disease.

Uses

Temporarily supports tissue elasticity and overall wellness during pregnancy.*

*CLAIMS BASED ON TRADITIONAL HOMEOPATHIC PRACTICE, NOT ACCEPTED MEDICAL EVIDENCE, NOT FDA EVALUATED.

This product is not intended to diagnose, treat, cure, or prevent any disease.

KEEP OUT OF REACH OF CHILDREN

Warnings and Storage:

Ask a professional before use if pregnant or breastfeeding or if you have severe symptoms. Keep away from children. If you have a reaction to this product that is not positive, discontinue use. Store in a cool and dry place.

Warnings and Storage:

Ask a professional before use if pregnant or breastfeeding or if you have severe symptoms. Keep away from children. If you have a reaction to this product that is not positive, discontinue use. Store in a cool and dry place.

*CLAIMS BASED ON TRADITIONAL HOMEOPATHIC PRACTICE, NOT ACCEPTED MEDICAL EVIDENCE, NOT FDA EVALUATED.

This product is not intended to diagnose, treat, cure, or prevent any disease.

Entire package label